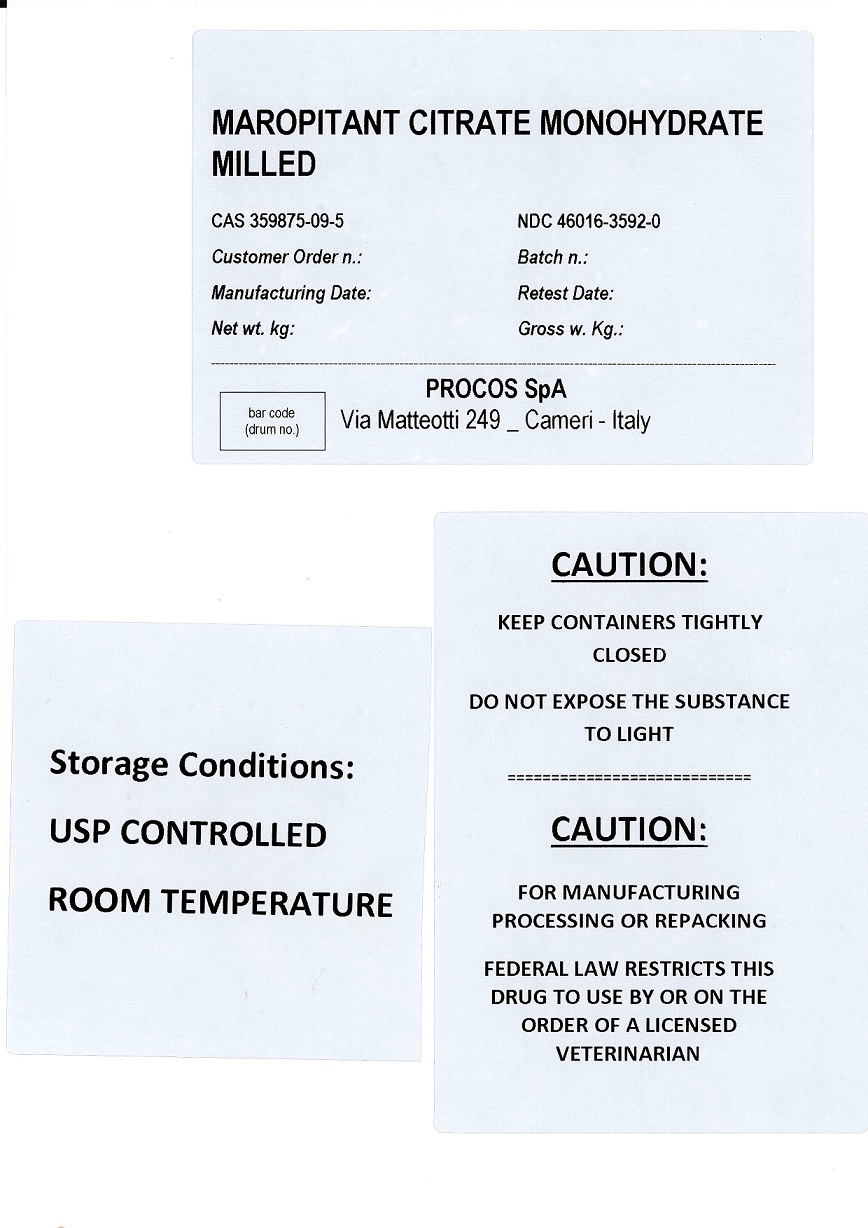 DRUG LABEL: maropitant citrate monohydrate
NDC: 46016-3592 | Form: POWDER
Manufacturer: Procos SpA
Category: other | Type: BULK INGREDIENT - ANIMAL DRUG
Date: 20231113

ACTIVE INGREDIENTS: MAROPITANT CITRATE 50 kg/50 kg

Maropitant Citrate Monohydrate milled

PACKAGE LABEL

MAROPITANT CITRATE MONOHYDRATE MILLEDCAS 359875-09-5 NDC 46016-3592-0
Batch n.:
Manufacturing Date: Retest Date:
Net wt. kg: Gross w. Kg.:
PROCOS SpA
Via Matteotti 249_Cameri - Italy
CAUTION: KEEP CONTAINERS TIGHTLY CLOSED
DO NOT EXPOSE THE SUBSTANCE TO LIGHT
CAUTION:
FOR MANUFACTURING, PROCESSING OR REPACKING
FEDERAL LAW RESTRICTS THIS DRUG TO USE BY OR ON THE ORDER OF A LICENSED VETERINARIAN
Storage Conditions: USP CONTROLLED ROOM TEMPERATURE